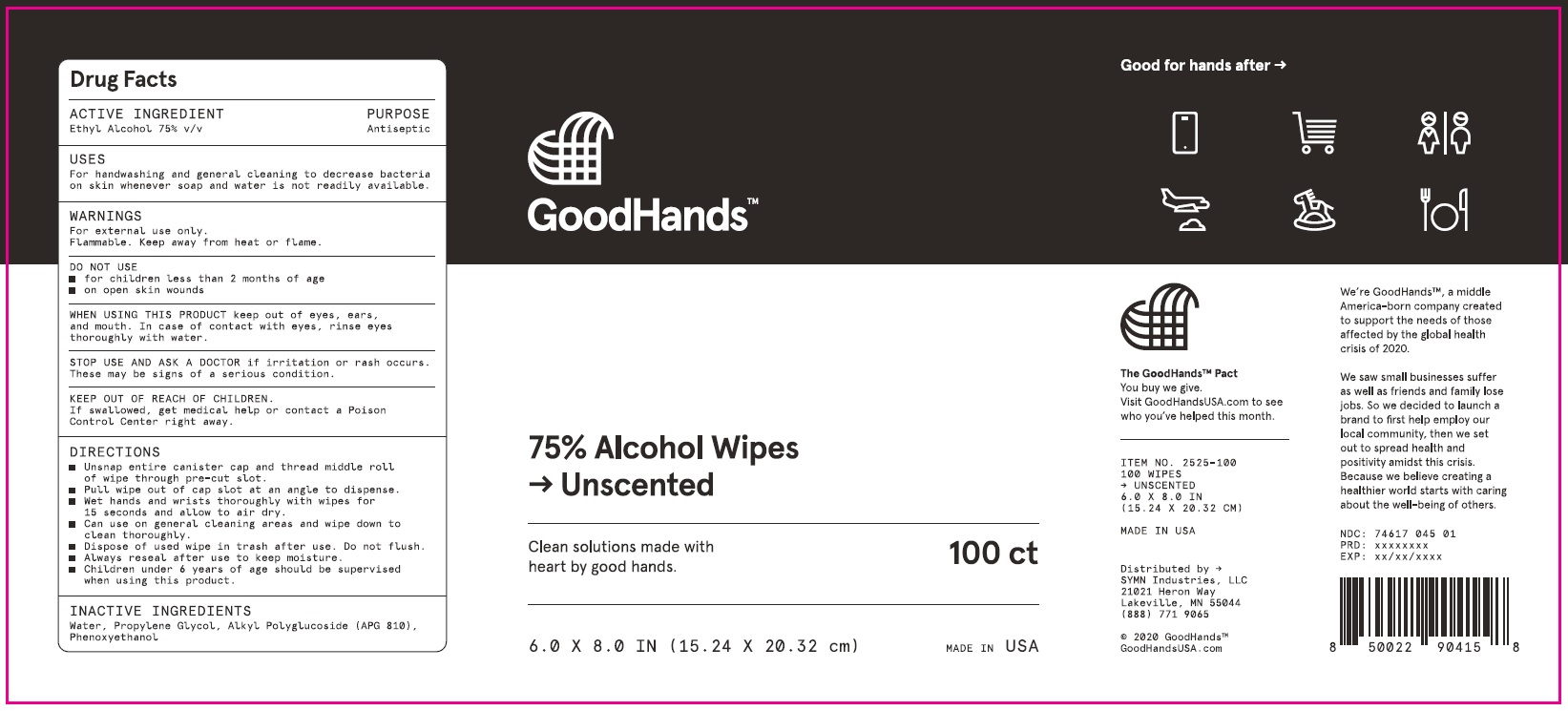 DRUG LABEL: Goodhands Alcohol Wipes
NDC: 74617-045 | Form: CLOTH
Manufacturer: SYMN Industries, LLC
Category: otc | Type: HUMAN OTC DRUG LABEL
Date: 20201022

ACTIVE INGREDIENTS: ALCOHOL 75 mL/100 mL
INACTIVE INGREDIENTS: PHENOXYETHANOL; PROPYLENE GLYCOL; WATER; CAPRYLYL/CAPRYL OLIGOGLUCOSIDE

Symn Industries Goodhands Alcohol Wipes

Active Ingredient

Ethyl Alcohol 75% v/v

Purpose

Antiseptic

Uses

For handwashing and general cleaning to decrease bacteria on skin whenever soap and water is not readily available.

Warnings

For external use only.

Flammable. Keep away from heat or flame

Do not use

- for children less than 2 months of age
- on open skin wounds

When using this product

keep out of eyes, ears, and mouth. In case of contact with eyes, rinse eyes thoroughly with water.

Stop use and ask a doctor

if irritation or rash occurs. These may be signs of a serious condition.

Keep out of reach of children.

If swallowed, get medical help or contact a Poison Control Center right away.

Directions

- Unsnap entire canister cap and thread middle roll of wipe through pre-cut slot.
- Pull wipe out of cap slot at an angle to dispense.
- Wet hands and wrists thoroughly with wipes for 15 seconds and allow to air dry.
- Can use on general cleaning areas and wipe down to clean thoroughly.
- Dispose of used wipe in trash after use. Do not flush.
- Always reseal after use to keep moisture.
- Children under 6 years of age should be supervised when using this product.

Inactive ingredients

Water, Propylene Glycol, Alkyl Polyglucoside (APG 810), Pehnoxyethanol

Company Information

Distributed by SYMN Industries, LLC

21021 Heron Way

Lakeville, MN 55044

(888) 771 9065

GoodHandsUSA.com

Package Label - Principal Display Panel

GoodHands

75% Alcohol Wipes

Unscented

Clean solutions made with heart by good hands.

100 ct

6.0 X 8.0 IN (15.24 X 20.32 cm)

MADE IN USA